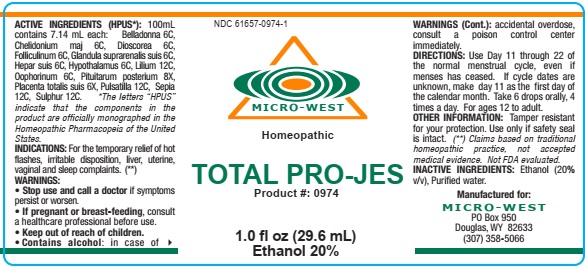 DRUG LABEL: TOTAL PRO-JES
NDC: 61657-0974 | Form: LIQUID
Manufacturer: White Manufacturing Inc. BDA Micro-West
Category: homeopathic | Type: HUMAN OTC DRUG LABEL
Date: 20210121

ACTIVE INGREDIENTS: PROGESTERONE 6 [hp_C]/30 mL; EPINEPHRINE 6 [hp_C]/30 mL; ATROPA BELLADONNA 6 [hp_C]/30 mL; CHELIDONIUM MAJUS 6 [hp_C]/30 mL; DIOSCOREA VILLOSA ROOT 6 [hp_C]/30 mL; ESTRONE 6 [hp_C]/30 mL; BOS TAURUS HYPOTHALAMUS 6 [hp_C]/30 mL; ARGININE 6 [hp_X]/30 mL; LILIUM LANCIFOLIUM FLOWERING TOP 12 [hp_C]/30 mL; MAMMAL LIVER 6 [hp_C]/30 mL; SUS SCROFA OVARY 6 [hp_C]/30 mL; BOS TAURUS PINEAL GLAND 6 [hp_X]/30 mL; BOS TAURUS PITUITARY GLAND 6 [hp_X]/30 mL; SUS SCROFA PLACENTA 6 [hp_X]/30 mL; PULSATILLA VULGARIS 12 [hp_C]/30 mL; SEPIA OFFICINALIS JUICE 12 [hp_C]/30 mL; SULFUR 12 [hp_C]/30 mL
INACTIVE INGREDIENTS: ALCOHOL

DRUG FACTS

ACTIVE INGREDIENTS

Belladonna 6C

Chelidonium maj 6C

Dioscorea 6C

Folliculinum 6C

Glandula suprarenalis suis 6C

Hepar Suis 6C

Hypothalamus 6C

Lilium 12C

Oophorinum 6C

Pituitarum posterium 8X

Placenta totalis suis 6X

Pulsatilla 12C

Sepia 12C

Sulphur 12C

INACTIVE INGREDIENTS

Alcohol (20% v/v)

Purified water

USES

hot flashes, irritable disposition, liver, uterine, vaginal and sleep complaints

KEEP OUT OF REACH OF CHILDREN

INDICATIONS

INDICATIONS: For the temporary relief of hot flashes, irritable disposition, liver, uterine, vaginal and sleep complaints.

WARNING

WARNING: STOP USE AND CALL A DOCTOR if symptoms persist or worsen. CONTAINS ALCOHOL: in case of accidental overdose, consult a poison control center immediately.

OTHER INFORMATION: Tamper resistant for your protection. Use only if safety seal is intact.

DIRECTIONS

DIRECTIONS:Use day 11 thru 22 of the normal menstrual cycle, even if menses has ceased. If cycle dates are unknown, make day 11 as the first day of the calendar month. Take 6 drops orally, 4 times a day. For ages 12 to adult.

PREGNANCY

IF PREGNANT OR BREAST FEEDING, consult a healthcare professional before use.

MANUFACTURE

MANUFACTURED FOR

MICRO-WEST

P.O. Box 950

DOUGLAS, WY 82633

1-307-358-5066

LABEL

NDC 61657-0974-1

MICRO-WEST

Homeopathic

TOTAL PRO-JES

Product #: 0974

1.0 fl oz (29.6 mL)

Ethanol 20%